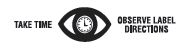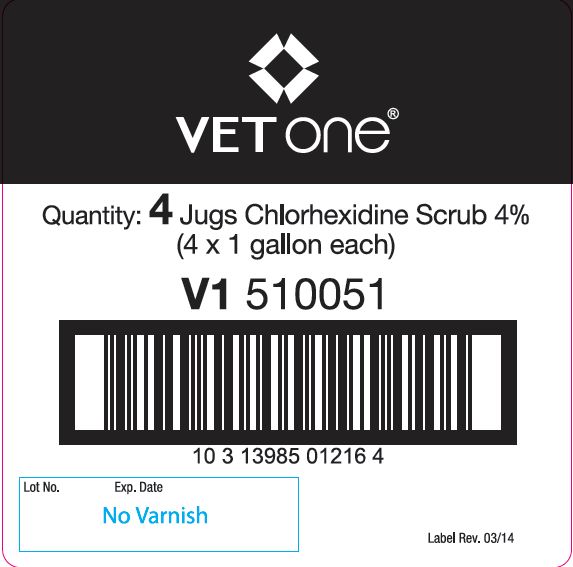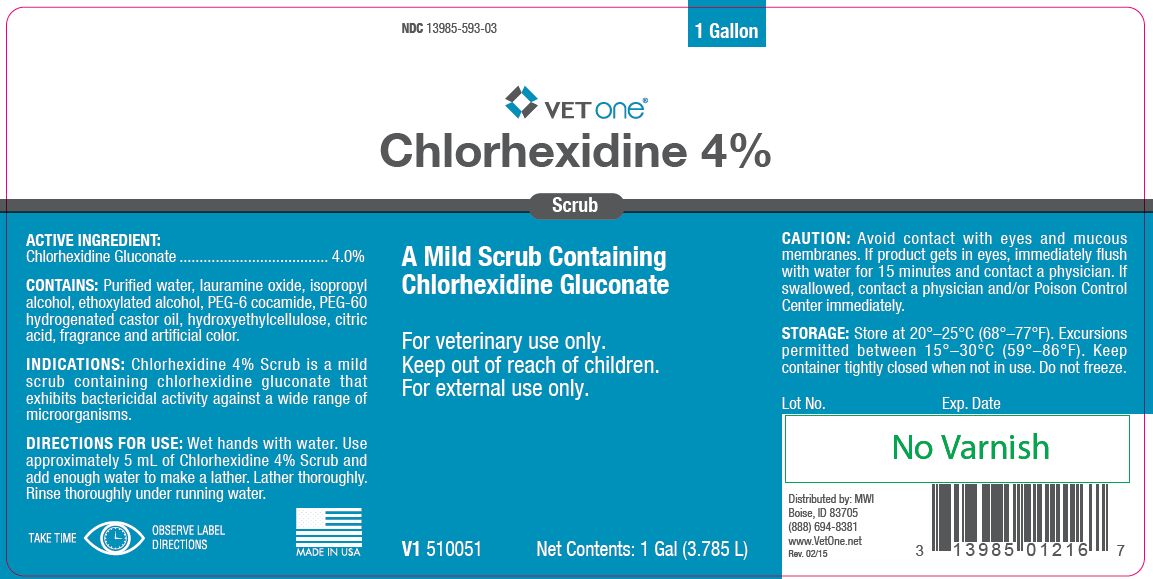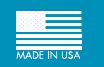 DRUG LABEL: Chlorhexidine 4%
NDC: 13985-593 | Form: LIQUID
Manufacturer: MWI
Category: animal | Type: OTC ANIMAL DRUG LABEL
Date: 20221114

ACTIVE INGREDIENTS: CHLORHEXIDINE GLUCONATE 214.5 g/1 L

Chlorhexidine 4% Scrub

PURPOSE

A Mild Scrub Containing Chlorhexidine Gluconate

WHEN USING

For veterinary use only.

Keep out of reach of children.

WHEN USING

For external use only.

ACTIVE INGREDIENT:

Chlorhexidine Gluconate ..................................... 4.0%

CONTAINS:

Purified water, lauramine oxide, isopropyl alcohol, ethoxylated alcohol, PEG-6 cocamide, PEG-60 hydrogenated castor oil, hydroxyethylcellulose, citric acid, fragrance and artificial color.

INDICATIONS:

Chlorhexidine 4% Scrub is a mild scrub containing chlorhexidine gluconate that exhibits bactericidal activity against a wide range of microorganisms.

DIRECTIONS FOR USE:

Wet hands with water. Use approximately 5 mL of Chlorhexidine 4% Scrub and add enough water to make a lather. Lather thoroughly. Rinse thoroughly under running water.

CAUTION:

Avoid contact with eyes and mucous membranes. If product gets in eyes, immediately flush with water for 15 minutes and contact a physician. If swallowed, contact a physician and/or Poison Control Center immediately.

STORAGE:

Store at 20°–25°C (68°–77°F). Excursions permitted between 15°–30°C (59°–86°F). Keep container tightly closed when not in use. Do not freeze.

Net Contents:

One Gallon (3.785 L) V1 510051

INFORMATION FOR OWNERS/CAREGIVERS

Distributed by: MWI
Boise, ID 83705
(888) 694-8381
www.VetOne.net